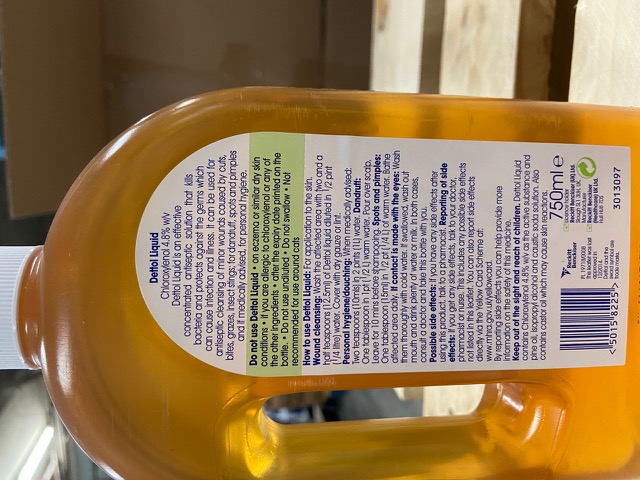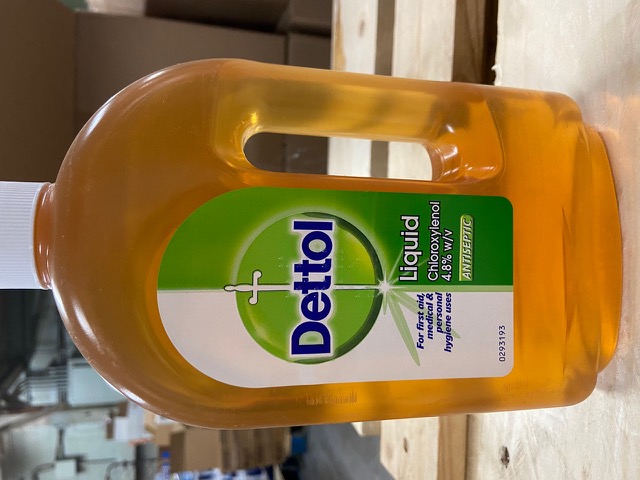 DRUG LABEL: Dettol First Aid Antiseptic
NDC: 79567-875 | Form: LIQUID
Manufacturer: Fresh N Clear LLC
Category: otc | Type: HUMAN OTC DRUG LABEL
Date: 20200728

ACTIVE INGREDIENTS: CHLOROXYLENOL 4.8 g/15 mL
INACTIVE INGREDIENTS: CARAMEL; WATER; WHITE PINE OIL; ISOPROPYL ALCOHOL

This is a hand sanitizer manufactured according to the Temporary Policy for Preparation of Certain Alcohol-Based Hand Sanitizer Products During the Public Health Emergency (CoViD-19); Guidance for Industry.

The hand sanitizer is manufactured using only the following United States Pharmacopoeia (USP) grade ingredients in the preparation of the product (percentage in final product formulation) consistent with World Health Organization (WHO) recommendations:

1. Isopropyl Alcohol (75%, v/v) in an aqueous solution denatured according to Alcohol and Tobacco Tax and Trade Bureau regulations in 27 CFR part 20.
2. Glycerol (1.45% v/v).
3. Hydrogen peroxide (0.125% v/v).
4. Sterile distilled water or boiled cold water.

The firm does not add other active or inactive ingredients. Different or additional ingredients may impact the quality and potency of the product.

Active Ingredient(s)

Chloroxylenol 4.8% w/v. Purpose: Antiseptic

Purpose

Antiseptic, Hand Sanitizer

Warnings

For external use only. Flammable. Keep away from heat or flame

Do not use

- in children less than 2 months of age
- on open skin wounds

WHEN USING

First Aid to help prevent infection of minocutsscrapesburns

Stop use and ask a doctor if irritation or rash occurs. These may be signs of a serious condition.

Keep out of reach of children. If swallowed, get medical help or contact a Poison Control Center right away.

Directions

- Place enough product on hands to cover all surfaces. Rub hands together until dry.
- Supervise children under 6 years of age when using this product to avoid swallowing.

Other information

- Store between 15-30C (59-86F)
- Avoid freezing and excessive heat above 40C (104F)

Inactive ingredients

glycerin, hydrogen peroxide, purified water USP

Package Label - Principal Display Panel

750ml NDC 79567-875-4